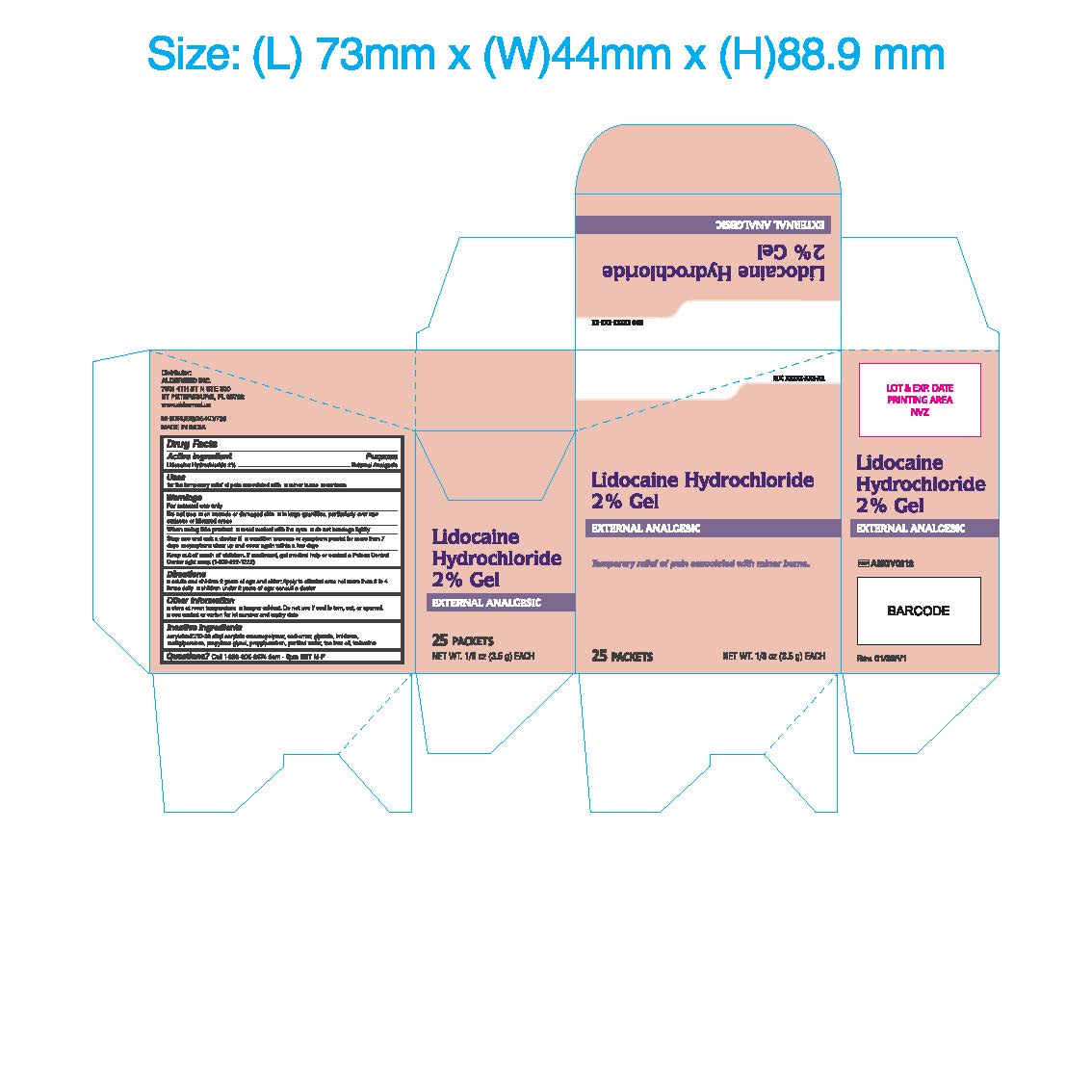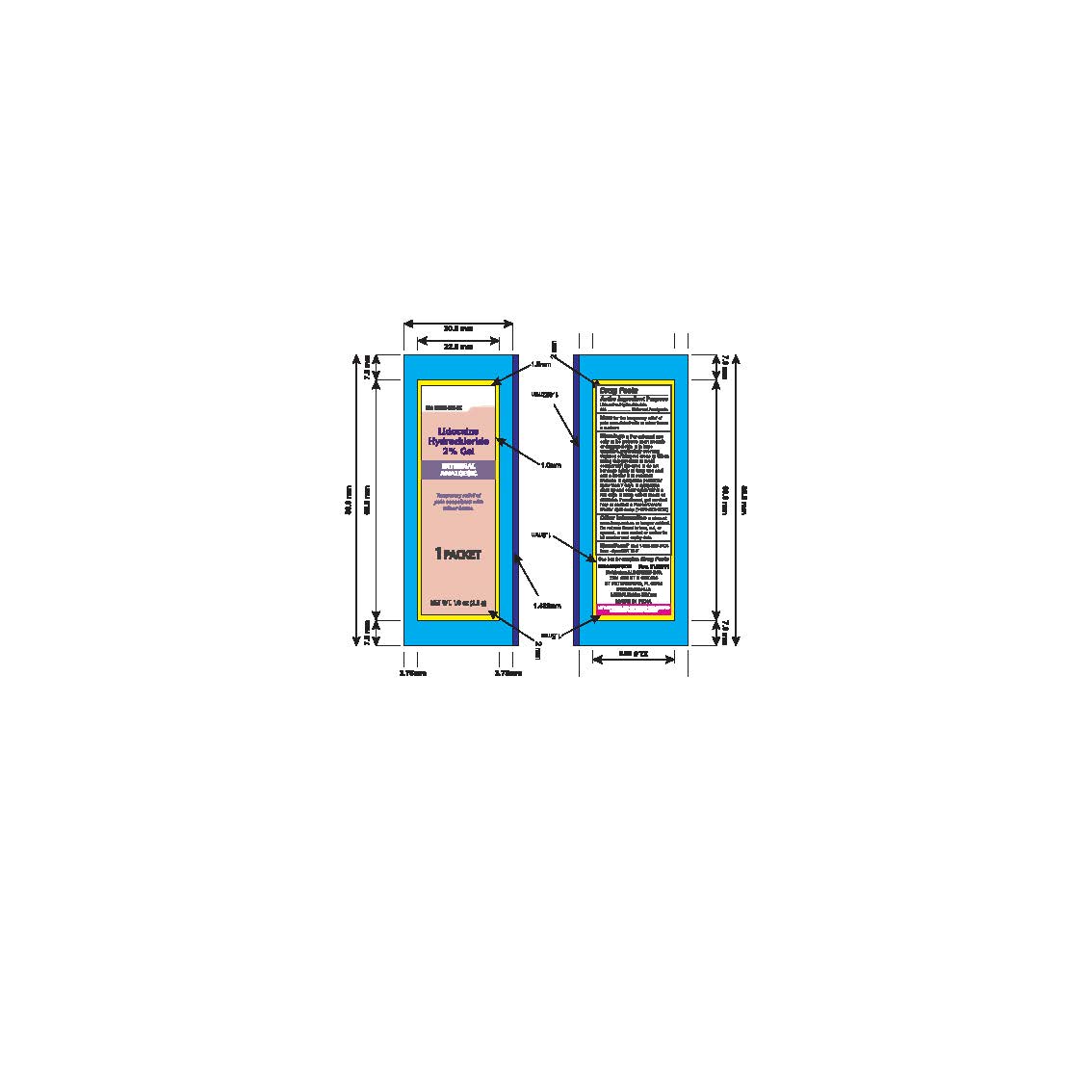 DRUG LABEL: Lidocaine Hydrochloride 2%
NDC: 87236-015 | Form: GEL
Manufacturer: Aldermed Inc.
Category: otc | Type: HUMAN OTC DRUG LABEL
Date: 20260212

ACTIVE INGREDIENTS: LIDOCAINE HYDROCHLORIDE 2 g/100 g
INACTIVE INGREDIENTS: TROLAMINE; METHYLPARABEN; GLYCERIN; IMIDUREA; PROPYLENE GLYCOL; PROPYLPARABEN; WATER; TEA TREE OIL; ACRYLATES/C10-30 ALKYL ACRYLATE CROSSPOLYMER (60000 MPA.S); CARBOMER 940

Lidocaine Hydrochloride 2% Gel

Active Ingredient

Lidocaine Hydrochloride 2%

Purpose

External Analgesic

Use(s)

■ For the temporary relief of pain associated with ■ Minor burns ■ Sunburn

Warnings

For External Use Only

Do not use

■ On wounds or damaged skin

■ In large quantities, particularly over raw surfaces or blistered areas

When using this product

■ Avoid contact with the eyes

■ Do not bandage tightly

Stop use and ask a doctor if

■ Condition worsens

■ Symptoms persist for more than 7 days

■ Symptoms clear up and occur again within a few days

Keep out of reach of children

If swallowed, get medical help or contact a Poison Control Center right away.(1-800-222-1222)

Directions

■ Adults and children 2 years of age and older: Apply to affected area not more than 3 to 4 times daily

■ Children under 2 years of age: Consult a doctor

Other Information

• Store at room temperature

• Tamper Evident. Do not use if seal is torn, cut, or opened.

- See sachet or cartonfor lot number and expiry date

Inactive Ingredients

Acrylates/C10-30 Alkyl Acrylate Crosscopolymer, Carbomer, Glycerin, Imidurea, Methylparaben, Propylene Glycol, Propylparaben, Purified Water, Tea Tree Leaf Oil, Trolamine

Questions?

Call 1-833-605-84-74 9am-5 pm EST M-F